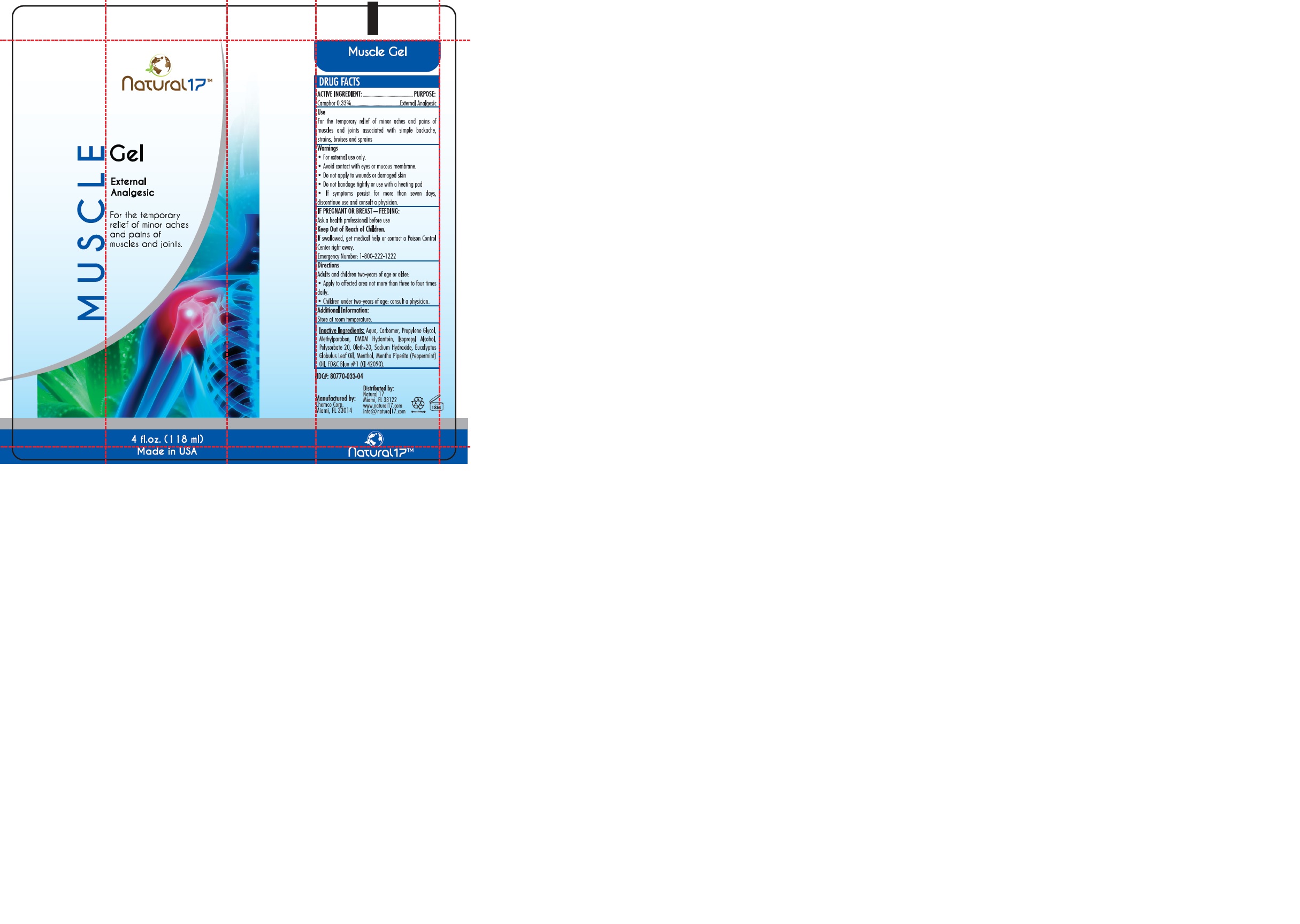 DRUG LABEL: NATURAL 17 MUSCLE
NDC: 80770-033 | Form: GEL
Manufacturer: NATURAL 17
Category: otc | Type: HUMAN OTC DRUG LABEL
Date: 20241122

ACTIVE INGREDIENTS: CAMPHOR (SYNTHETIC) 0.33 g/100 mL
INACTIVE INGREDIENTS: PROPYLENE GLYCOL; ISOPROPYL ALCOHOL; EUCALYPTUS GLOBULUS LEAF; METHYLPARABEN; BASIC BLUE 1; WATER; CARBOMER 940; DMDM HYDANTOIN; POLYSORBATE 20; SODIUM HYDROXIDE; OLETH-20; MENTHA ARVENSIS FLOWER OIL

80770-033-04

ACTIVE INGREDIENT

Camphor …………………….……………….………….………0.33 %

PURPOSE

External Analgesic

USES:

For the temporary relief of minor aches and pains of muscles and joints associated with simple backache, arthritis, strains, bruises and sprains

WARNINGS

For external use only.
Avoid contact with eyes or mucous membrane.
Do not apply to wounds or damaged skin
Do not bandage tightly or use with a heating pad

If symptoms persist for more than seven days, discontinue use and consult a physician.

KEEP OUT OF REACH OF CHILDREN

If swallowed, get medical help or contact a Poison Control Center right away.

Emergency Number: 1-800-222-1222

PREGNANCY OR BREAST FEEDING

Ask a health professional before use.

DIRECTIONS:

Adults and children two-years of age or older:

Apply to affected area not more than three to four times daily.

Children under two-years of age: consult a physician.

Additional Information:

Store at room temperature.

INACTIVE INGREDIENT

Aqua, Carbomer, Propylene Glycol, Methylparaben, DMDM Hydantoin, Isopropyl Alcohol, Polysorbate 20, Oleth-20, Sodium Hydroxide, Eucalyptus Globulus Leaf Oil, Menthol, Mentha Piperita (Peppermint) Oil, FD&C Blue #1 (CI 42090).